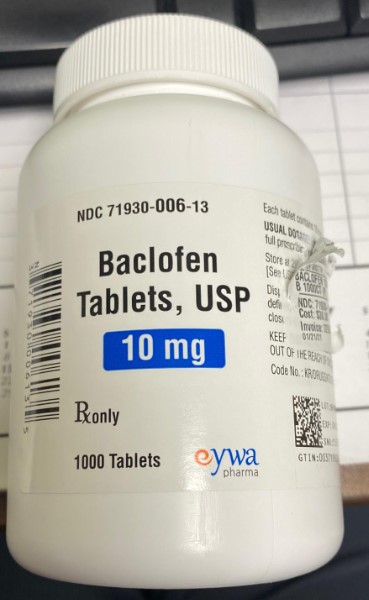 DRUG LABEL: Baclofen
NDC: 80175-0006 | Form: TABLET
Manufacturer: Central Packaging
Category: prescription | Type: HUMAN PRESCRIPTION DRUG LABEL
Date: 20210222

ACTIVE INGREDIENTS: BACLOFEN 10 mg/1 1

INDICATIONS AND USAGE

Baclofen Tablets, USP are useful for the alleviation of signs and symptoms of spasticity resulting from multiple sclerosis, particularly for the relief of flexor spasms and concomitant pain, clonus, and muscular rigidity.
Patients should have reversible spasticity so that baclofen treatment will aid in restoring residual function. Baclofen Tablets, USP may also be of some value in patients with spinal cord injuries and other spinal cord diseases.

Baclofen Tablets, USP are not indicated in the treatment of skeletal muscle spasm resulting from rheumatic disorders.
The efficacy of baclofen in stroke, cerebral palsy, and Parkinson’s disease has not been established and, therefore, it is not recommended for these conditions.